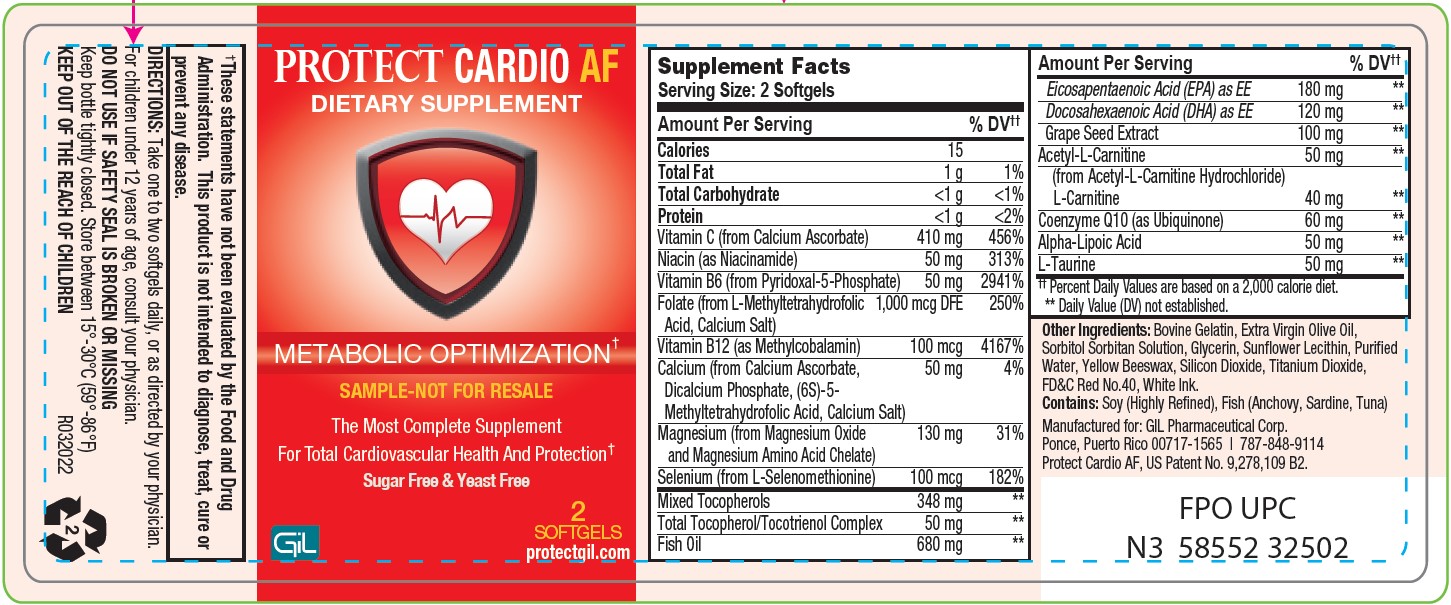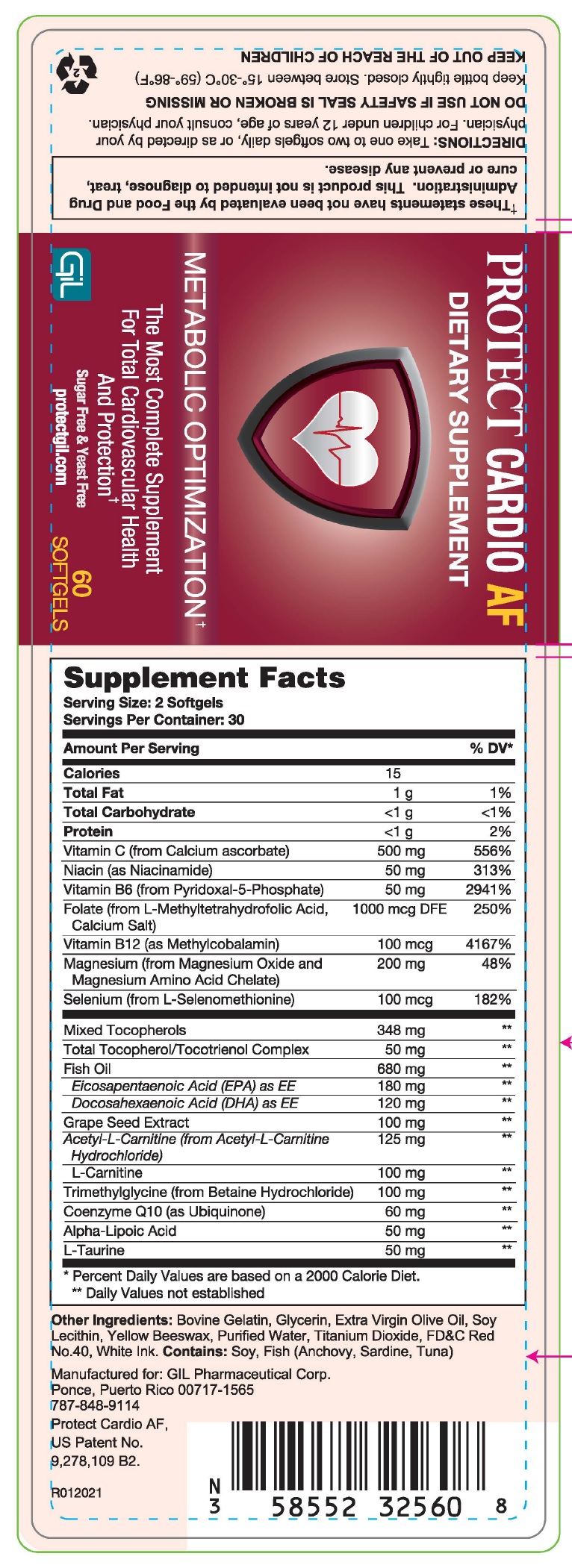 DRUG LABEL: PROTECT CARDIO AF
NDC: 58552-325 | Form: CAPSULE
Manufacturer: GIL Pharmaceutical Corp.
Category: other | Type: DIETARY SUPPLEMENT
Date: 20221107

ACTIVE INGREDIENTS: ASCORBIC ACID 500 mg/1 1; NIACIN 50 mg/1 1; PYRIDOXINE 50 mg/1 1; FOLIC ACID 1 mg/1 1; METHYLCOBALAMIN 0.1 mg/1 1; MAGNESIUM 200 mg/1 1; SELENIUM 0.1 mg/1 1; TOCOPHEROL 348 mg/1 1; TOCOTRIENOL 50 mg/1 1; FISH OIL 680 mg/1 1; ICOSAPENT 180 mg/1 1; DOCONEXENT 120 mg/1 1; VITIS VINIFERA SEED 100 mg/1 1; ACETYLCARNITINE 125 mg/1 1; LEVOCARNITINE 100 mg/1 1; BETAINE 100 mg/1 1; UBIDECARENONE 60 mg/1 1; ALPHA LIPOIC ACID 50 mg/1 1; TAURINE 50 mg/1 1
INACTIVE INGREDIENTS: ALPHA-LACTALBUMIN (BOVINE); GLYCERIN; OLIVE OIL; LECITHIN, SOYBEAN; YELLOW WAX; WATER; TITANIUM DIOXIDE; FD&C RED NO. 40

PROTECT CARDIO AF
DIETARY SUPPLEMENT

STATEMENT OF IDENTITY

METABOLIC OPTIMIZATION†

The Most Complete Supplement For Total Cardiovascular Health and Protection†

Sugar Free & Yeast Free

SUPPLEMENT FACTS

Serving Size 2 Softgels

Servings Per Container: 30

Amount Per Serving | %DV
Calories | 15
Total Fat | 1g | 1%
Total Carbohydrate | <1 g | <1%
Protein | <1 g | 2%
Vitamin C (from Calcium ascorbate) | 500 mg | 556%
Niacin (as Niacinamide) | 50 mg | 313%
Vitamin B6 (from Pyridoxal-5-Phosphate) | 50 mg | 2941%
Folate (from L-Methyltetrahydrofolic Acid, Calcium Salt) | 1000 mcg DFE | 250%
Vitamin B12 (as Methylcobalamin) | 100 mcg | 4167%
Magnesium (from Magnesium Oxide and Magnesium Amino Acid Chelate) | 200 mg | 48%
Selenium (from L-Selenomethionine) | 100 mcg | 182%
Mixed Tocopherols | 348 mg | **
Total Tocopherol/Tocotrienol Complex | 50 mg | **
Fish Oil | 680 mg | **
Eicosapentaenoic Acid (EPA) as EE | 180 mg | **
Docosahexaenoic Acid (DHA) as EE | 120 mg | **
Grape Seed Extract | 100 mg | **
Acetyl-L-Carnilite (from Acetyl-L-Carnilite Hydrochloride) | 125 mg | **
L- Carnilite | 100 mg | **
Trimethylglycine (from Betaine Hydrochloride) | 100 mg | **
Coenzyme Q10 (as Ubiquinone) | 60 mg | **
Alpha-Lipoic Acid | 50 mg | **
L-Taurine | 50 mg | **
*Percent Dally Values are based on a 2000 Calorie Diet.
**Daily Value not established.

Other Ingredients

Bovine Gelatin, Glycerin, Extra Virgin Olive Oil, Soy Lecithin, Yellow Beeswax, Purified Water, Titanium Dioxide, FD&C Red No.40, White Ink. Contains: Soy, Fish (Anchovy, Sardine, Tuna)

WARNINGS

These statements have not been evaluated by the Food and Drug Administration. This product is not intended to diagnose, treat, cure or prevent any disease.

DOSAGE AND ADMINISTRATION

DIRECTIONS: Take one to two softgels daily, or as directed by your physician. For children under 12 years of age, consult your physician.

DO NOT USE IF SAFETY SEAL IS BROKEN OR MISSING

Keep bottle tightly closed. Store between 15o-30oC (59o-86oF)

KEEP OUT OF THE REACH OF CHILDREN

Manufactured for:

GIL Pharmaceutical Corp.

Ponce, Puerto Rico 00717-1565

787-848-9114

Protect Cardio AF,

US Patent No.

9,278,109 B2.

R012021

PACKAGE LABEL.PRINCIPAL DISPLAY PANEL

PROTECT CARDIO AF Dietary supplement NDC - 58552-325-60- 60 Capsules- Label

PROTECT CARDIO AF Dietary supplement NDC - 58552-325-02- 2 Capsules- Label